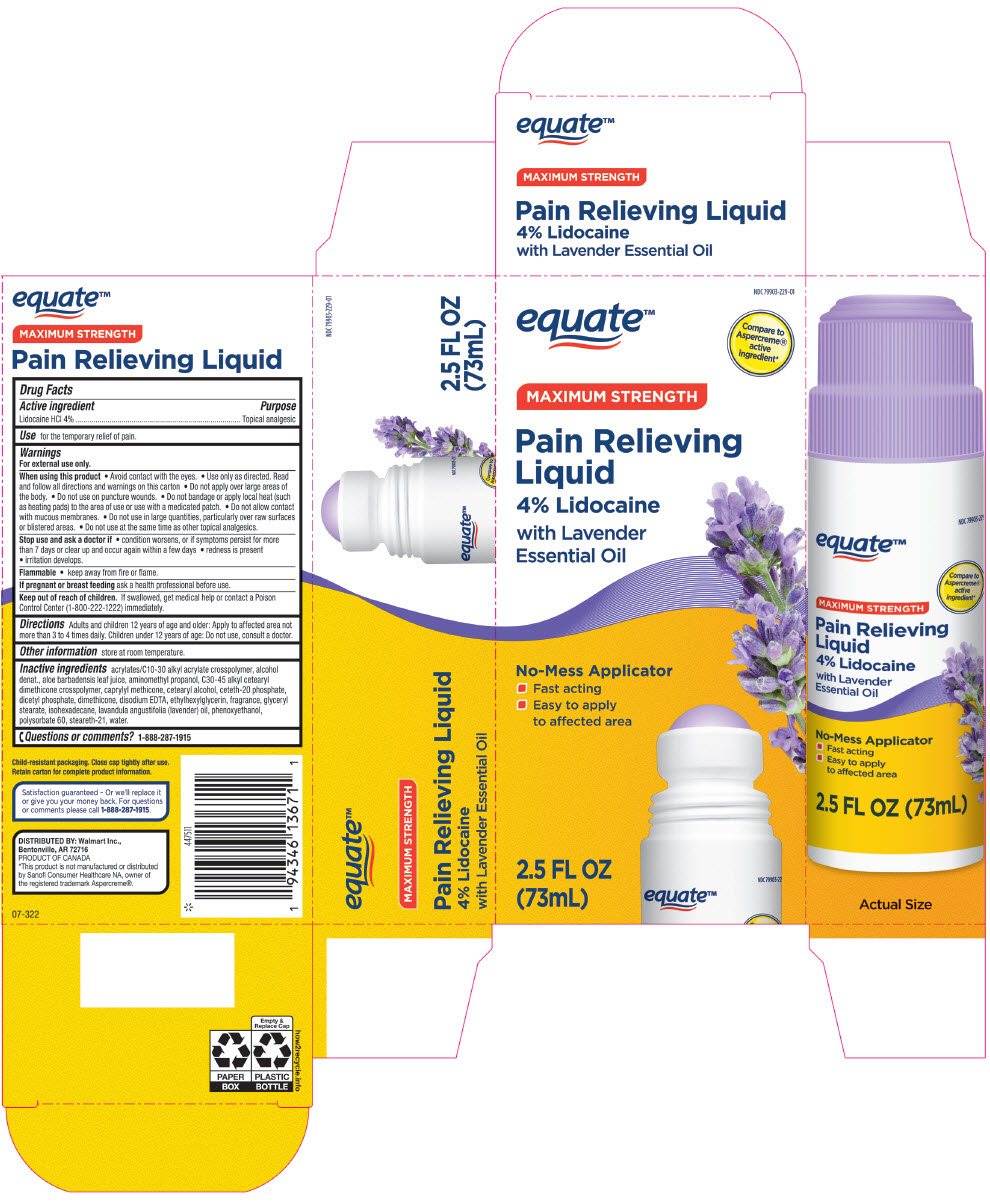 DRUG LABEL: equate Maximum Strength Pain Relieving 4% Lidocaine with Lavender Essential Oil
NDC: 79903-229 | Form: LIQUID
Manufacturer: Wal-Mart Stores, Inc.
Category: otc | Type: HUMAN OTC DRUG LABEL
Date: 20231221

ACTIVE INGREDIENTS: LIDOCAINE HYDROCHLORIDE 40 mg/1 mL
INACTIVE INGREDIENTS: ALCOHOL; ALOE VERA LEAF; AMINOMETHYLPROPANOL; C30-45 Alkyl Cetearyl Dimethicone Crosspolymer; CAPRYLYL TRISILOXANE; CETOSTEARYL ALCOHOL; Ceteth-20 Phosphate; DIHEXADECYL PHOSPHATE; Dimethicone; EDETATE DISODIUM; Ethylhexylglycerin; GLYCERYL MONOSTEARATE; Isohexadecane; LAVENDER OIL; PHENOXYETHANOL; Polysorbate 60; Steareth-21; Water

equate™ Maximum Strength Pain Relieving Liquid 4% Lidocaine with Lavender Essential Oil
Topical analgesic

Drug Facts

Active ingredient

Lidocaine HCl 4%

Purpose

Topical analgesic

Use

for the temporary relief of pain.

Warnings

For external use only.

When using this product

- Avoid contact with the eyes.
- Use only as directed. Read and follow all directions and warnings on this carton
- Do not apply over large areas of the body.
- Do not use on puncture wounds.
- Do not bandage or apply local heat (such as heating pads) to the area of use or use with a medicated patch.
- Do not allow contact with mucous membranes.
- Do not use in large quantities, particularly over raw surfaces or blistered areas.
- Do not use at the same time as other topical analgesics.

Stop use and ask a doctor if

- condition worsens, or if symptoms persist for more than 7 days or clear up and occur again within a few days
- redness is present
- irritation develops.

Flammable

- keep away from fire or flame.

PREGNANCY OR BREAST FEEDING

If pregnant or breast feeding ask a health professional before use.

Keep out of reach of children. If swallowed, get medical help or contact a Poison Control Center (1-800-222-1222) immediately.

Directions

Adults and children 12 years of age and older: Apply to affected area not more than 3 to 4 times daily. Children under 12 years of age: Do not use, consult a doctor.

Other information

store at room temperature.

Inactive ingredients

acrylates/C10-30 alkyl acrylate crosspolymer, alcohol denat., aloe barbadensis leaf juice, aminomethyl propanol, C30-45 alkyl cetearyl dimethicone crosspolymer, caprylyl methicone, cetearyl alcohol, ceteth-20 phosphate, dicetyl phosphate, dimethicone, disodium EDTA, ethylhexylglycerin, fragrance, glyceryl stearate, isohexadecane, lavandula angustifolia (lavender) oil, phenoxyethanol, polysorbate 60, steareth-21, water.

Questions or comments?

1-888-287-1915

DISTRIBUTED BY: Walmart Inc.,
Bentonville, AR 72716

PRINCIPAL DISPLAY PANEL - 73 mL Bottle Carton

NDC 79903-229-01

equate™

Compare to
Aspercreme®
active
ingredient*

MAXIMUM STRENGTH

Pain Relieving
Liquid
4% Lidocaine
with Lavender
Essential Oil

No-Mess Applicator

- Fast acting
- Easy to apply
  to affected area

2.5 FL OZ
(73mL)